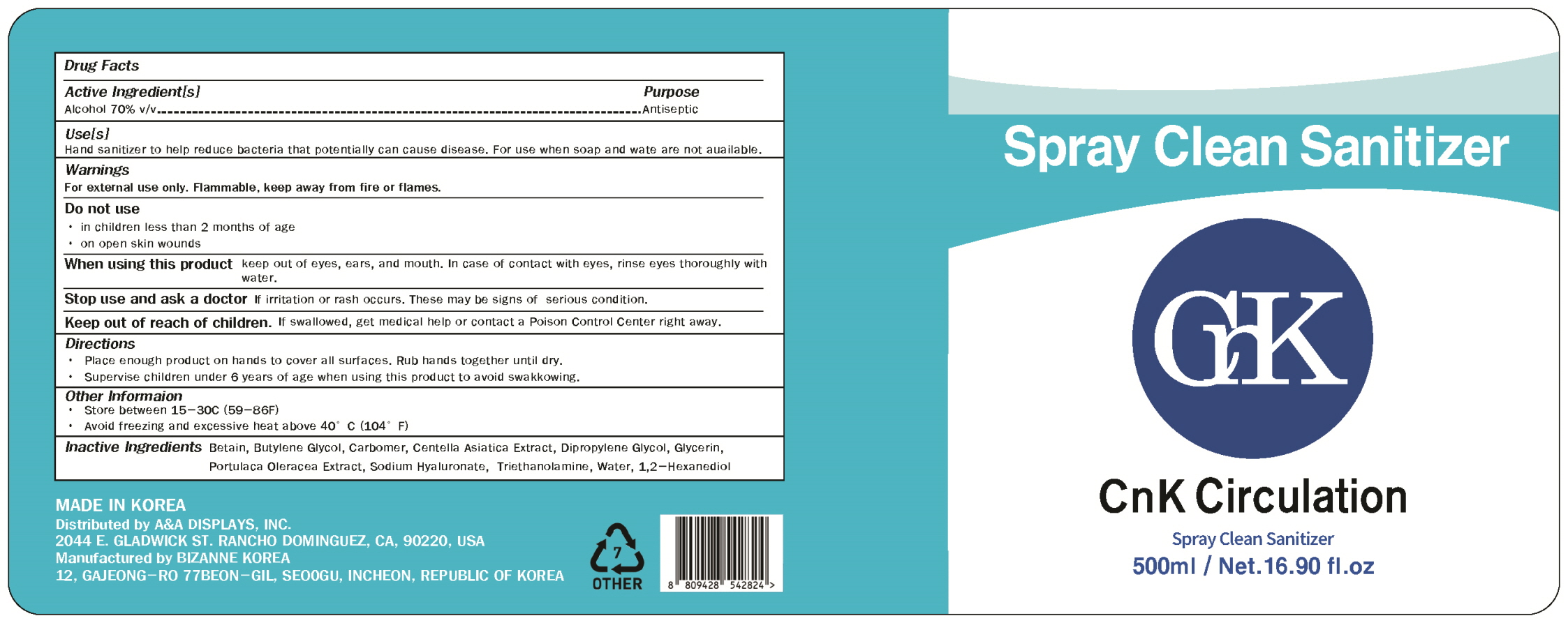 DRUG LABEL: UNIVIS POCKET CLEAN SANITIZING WIPES
NDC: 79398-0010 | Form: CLOTH
Manufacturer: Lance Global Gimpo Branch
Category: otc | Type: HUMAN OTC DRUG LABEL
Date: 20200828

ACTIVE INGREDIENTS: ALCOHOL 3.627 g/100 1
INACTIVE INGREDIENTS: WATER; CETYLPYRIDINIUM CHLORIDE; HYDROXYACETOPHENONE

Lance Global Gimpo Branch

ACTIVE INGREDIENT

Alcohol

INACTIVE INGREDIENT

1,2-hexanediol, betaine, butylene glycol, carbomer, centella asiatica extract, dipropylene glycol, glycerin, portulaca oleracea extract, sodium hyaluronate, triethanolamine, water,

PURPOSE

Antiseptic

keep out of reach of the children

INDICATIONS AND USAGE

Please enough product on hands to cover all surfaces. Rub hands together until dry.

Supervise children under 6 years of age when using this product to avoid swakkkowing.

WARNINGS

For external use only. Flammable, keep away from fire or flames.

Do not use

- in children less than 2 months of age
- on open skin wounds

When using this product keep out of eyes, ears, and mouth. In case of contact with eyes, rinse eyes thoroughly with water.

Stop use and ask a doctor if irritation or rash occurs. These may be signs of serious condition.

Keep out of reach of children. If swallowed, get medical help or contact a Poison Control Center right away.

DOSAGE AND ADMINISTRATION

for external use only